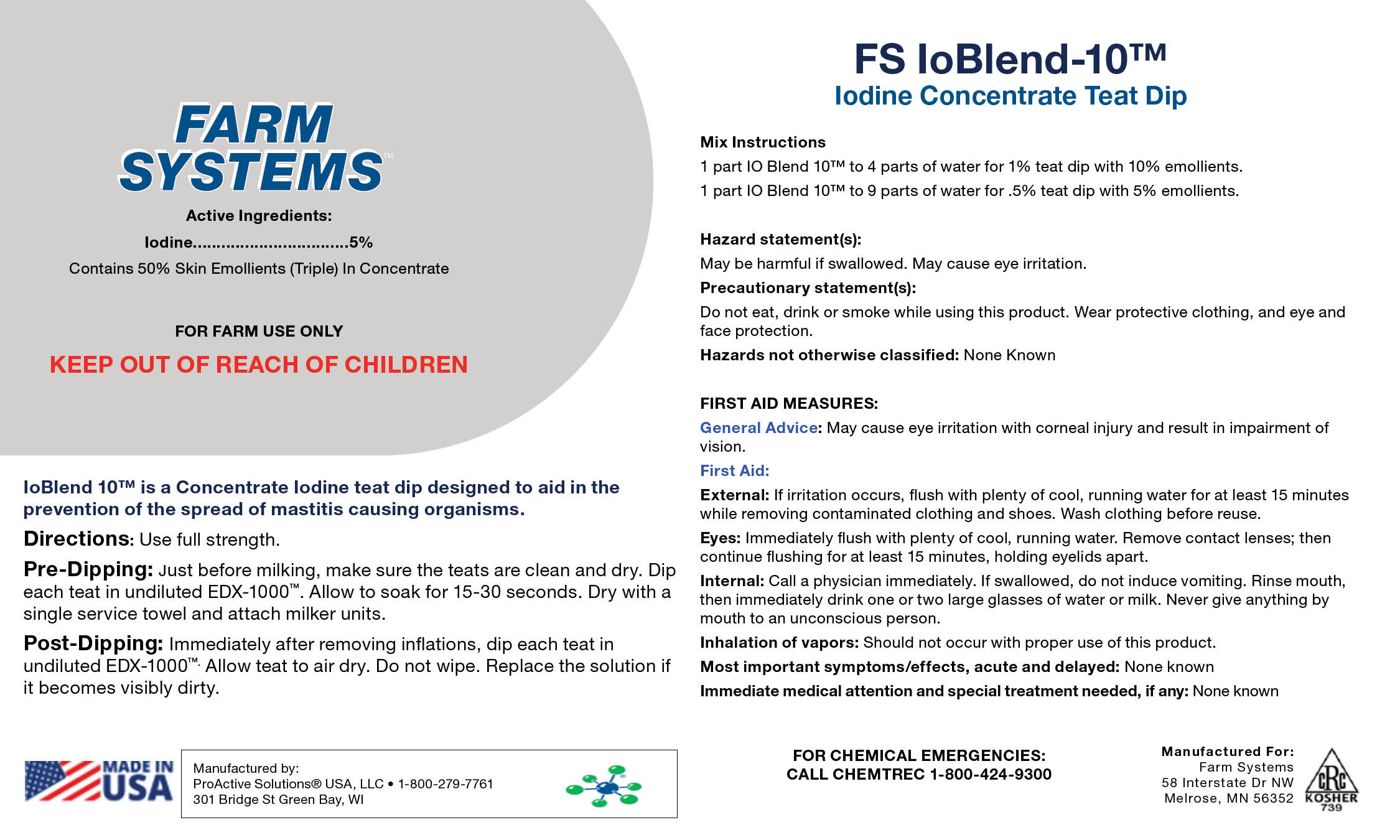 DRUG LABEL: FS IoBlend 10
NDC: 86193-4666 | Form: SOLUTION
Manufacturer: Genex Cooperative, Inc.
Category: animal | Type: OTC ANIMAL DRUG LABEL
Date: 20240404

ACTIVE INGREDIENTS: IODINE 5 kg/1 kg

FS IoBlend 10

FS IoBlend10

Mix Instructions
1 part IO Blend 10™ to 4 parts of water for 1% teat dip with 10% emollients.
1 part IO Blend 10™ to 9 parts of water for .5% teat dip with 5% emollients.
Hazard statement(s):
May be harmful if swallowed. May cause eye irritation.
Precautionary statement(s):
Do not eat, drink or smoke while using this product. Wear protective clothing, and eye and face protection.
Hazards not otherwise classified: None Known
FIRST AID MEASURES:
General Advice: May cause eye irritation with corneal injury and result in impairment of vision.
First Aid:
External: If irritation occurs, flush with plenty of cool, running water for at least 15 minutes while removing contaminated clothing and shoes. Wash clothing before reuse.
Eyes: Immediately flush with plenty of cool, running water. Remove contact lenses; then continue flushing for at least 15 minutes, holding eyelids apart.
Internal: Call a physician immediately. If swallowed, do not induce vomiting. Rinse mouth, then immediately drink one or two large glasses of water or milk. Never give anything by mouth to an unconscious person.
Inhalation of vapors: Should not occur with proper use of this product.
Most important symptoms/effects, acute and delayed: None known
Immediate medical attention and special treatment needed, if any: None known

IoBlend 10™ is a Concentrate Iodine teat dip designed to aid in the prevention of the spread of mastitis causing organisms.
Directions: Use full strength.
Pre-Dipping: Just before milking, make sure the teats are clean and dry. Dip each teat in undiluted EDX-1000™. Allow to soak for 15-30 seconds. Dry with a single service towel and attach milker units.
Post-Dipping: Immediately after removing inflations, dip each teat in undiluted EDX-1000™. Allow teat to air dry. Do not wipe. Replace the solution if it becomes visibly dirty.

FOR CHEMICAL EMERGENCIES: CALL CHEMTREC 1-800-424-9300